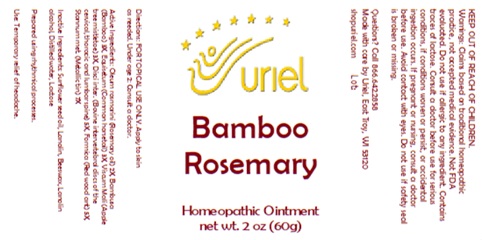 DRUG LABEL: Bamboo Rosemary
NDC: 48951-2162 | Form: OINTMENT
Manufacturer: Uriel Pharmacy, Inc
Category: homeopathic | Type: HUMAN OTC DRUG LABEL
Date: 20251010

ACTIVE INGREDIENTS: BAMBUSA VULGARIS WHOLE 3 [hp_X]/1 g; EQUISETUM ARVENSE TOP 3 [hp_X]/1 g; ROSEMARY OIL 2 [hp_X]/1 g; TIN 7 [hp_X]/1 g; FORMICA RUFA 5 [hp_X]/1 g; VISCUM ALBUM FRUITING TOP 3 [hp_X]/1 g; BOS TAURUS INTERVERTEBRAL DISC 5 [hp_X]/1 g
INACTIVE INGREDIENTS: BEESWAX; WATER; LACTOSE; LANOLIN; LANOLIN ALCOHOL; SUNFLOWER OIL

Bamboo Rosemary

INDICATIONS AND USAGE

Directions: FOR TOPICAL USE ONLY.

DOSAGE AND ADMINISTRATION

Apply to skin as needed. Under age 2: Consult a doctor.

ACTIVE INGREDIENT

Active Ingredients: Oleum rosmarini (Rosemary oil) 2X, Bambusa (Bamboo) 3X, Equisetum (Common horsetail) 3X, Viscum Mali (Apple tree mistletoe) 3X, Disci inter. (Bovine intervertebral discs of the cervical, thoracic and lumbar spine) 5X, Formica (Red wood ant) 5X, Stannum met. (Metallic tin) 7X

INACTIVE INGREDIENT

Inactive Ingredients: Sunflower seed oil, Lanolin, Beeswax, Lanolin alcohol, Distilled water, Lactose

Prepared using rhythmical processes.

PURPOSE

Use: Temporary relief of headache.

KEEP OUT OF REACH OF CHILDREN.

WARNINGS

Warnings: Claims based on traditional homeopathic practice, not accepted medical evidence. Not FDA evaluated. Do not use if allergic to any ingredient. Contains traces of lactose. Consult a doctor before use for serious conditions, if conditions worsen or persist, or accidental ingestion occurs. If pregnant or nursing, consult a doctor before use. Avoid contact with eyes. Do not use if safety seal is broken or missing.

Questions? Call 866.642.2858
Made with care by Uriel, East Troy, WI 53120
shopuriel.com Lot: